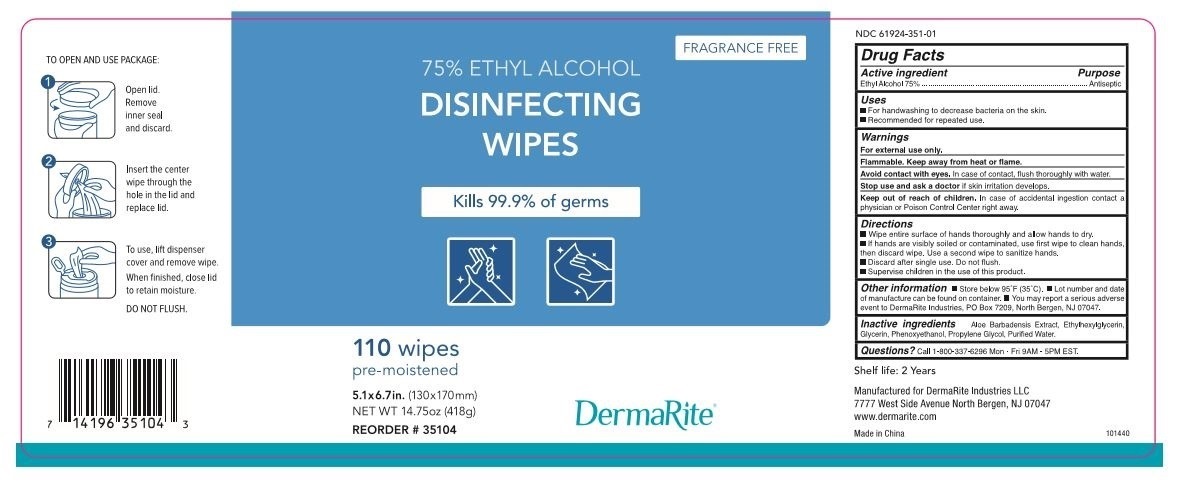 DRUG LABEL: 75% Ethyl Alcohol Disinfecting Wipes
NDC: 61924-351 | Form: CLOTH
Manufacturer: DERMARITE INDUSTRIES LLC
Category: otc | Type: HUMAN OTC DRUG LABEL
Date: 20220113

ACTIVE INGREDIENTS: ALCOHOL 75 g/100 g
INACTIVE INGREDIENTS: WATER; ALOE VERA LEAF; PROPYLENE GLYCOL; GLYCERIN; ETHYLHEXYLGLYCERIN

75% Ethyl Alcohol Disinfecting Wipes

Active Ingredient(s)

Alcohol 75% Purpose: Antiseptic

Purpose

Antiseptic, Hand Sanitizer

Use

For handwashing to decrease bacteria on the skin.

Recommended for repeated use.

Warnings

For external use only.

Flammable. Keep away from heat or flame.

Avoid contact with eyes. In case of contact, flush thoroughly with water.

Stop use and ask a doctor if skin irritation develops.

Keep out of reach of children. In case of accidential ingestion contact a physician or Poison control Ceter right away.

Directions

- Wipe entiere surface of hands thoroughly and allow hands to dry.
- If hands are visibly soiled or contaminated, use first wipe to clean hands, then discard wipe. use a second wipe to sanitize hands.
- Discard after single use. Do not flush.
- Supervise children in the use of this product.

Other information

- Store below 95F (35C)
- Lot number and date of manufacture can be found on container.
- You may report a serious adverse event to DermaRite Industries, PO Box 7209, North bergen, NJ 07047

Inactive ingredients

Aloe Barbadensis Extract, Ethylhexylglycerine, Glycerine, Phenoxyethanol, Propylene Glycol, Purified Water

Questions?

Call 1-800-337-6296 Mon-fri 9 AM-5 PM EST.

Keep Out of Reach of Children Section

In case of accidental ingestion contact a physician or Poison Control Center right away.

KEEP OUT OF REACH OF CHILDREN

In case of accidental ingestion contact a physican or poison control center right away.